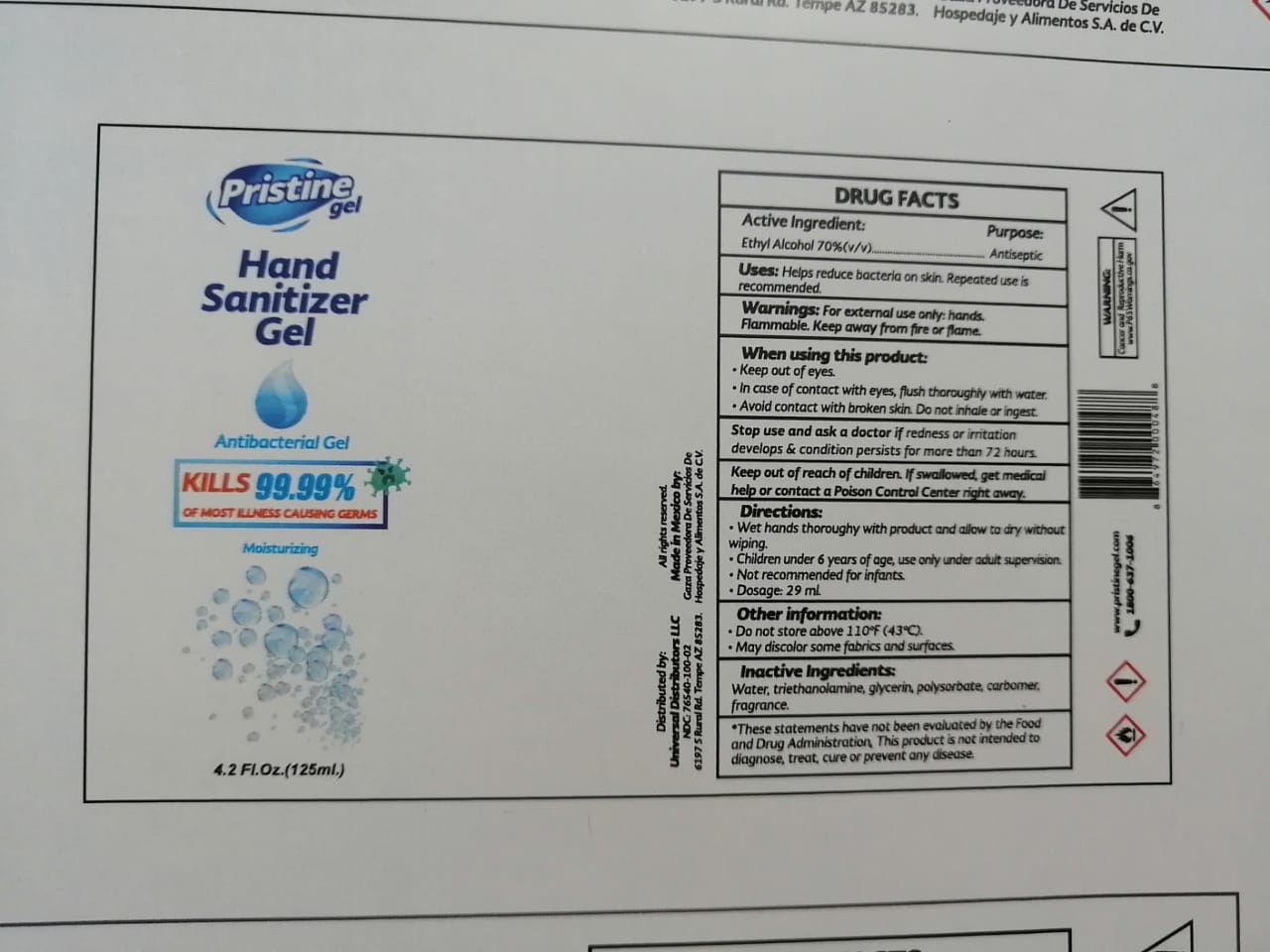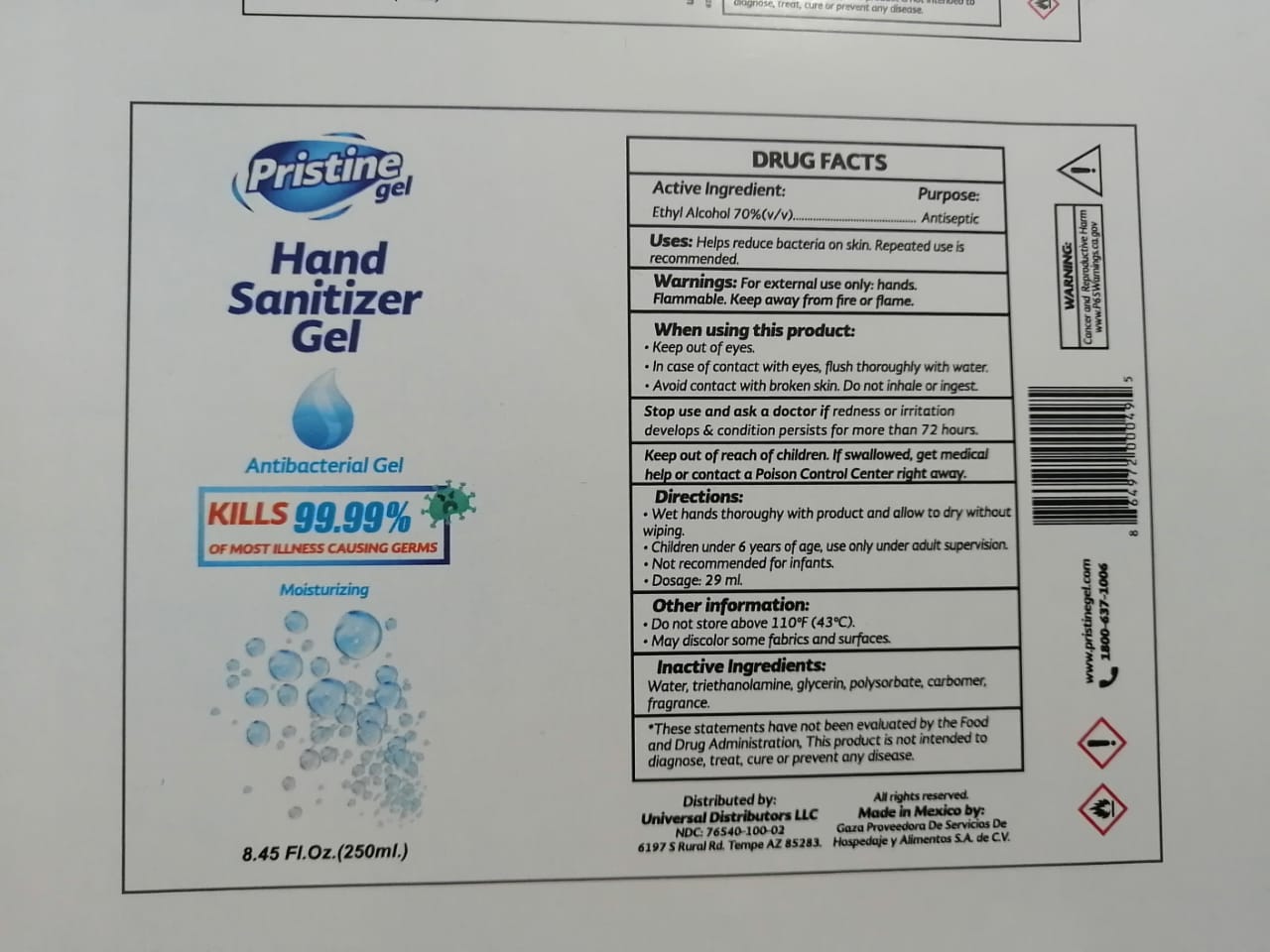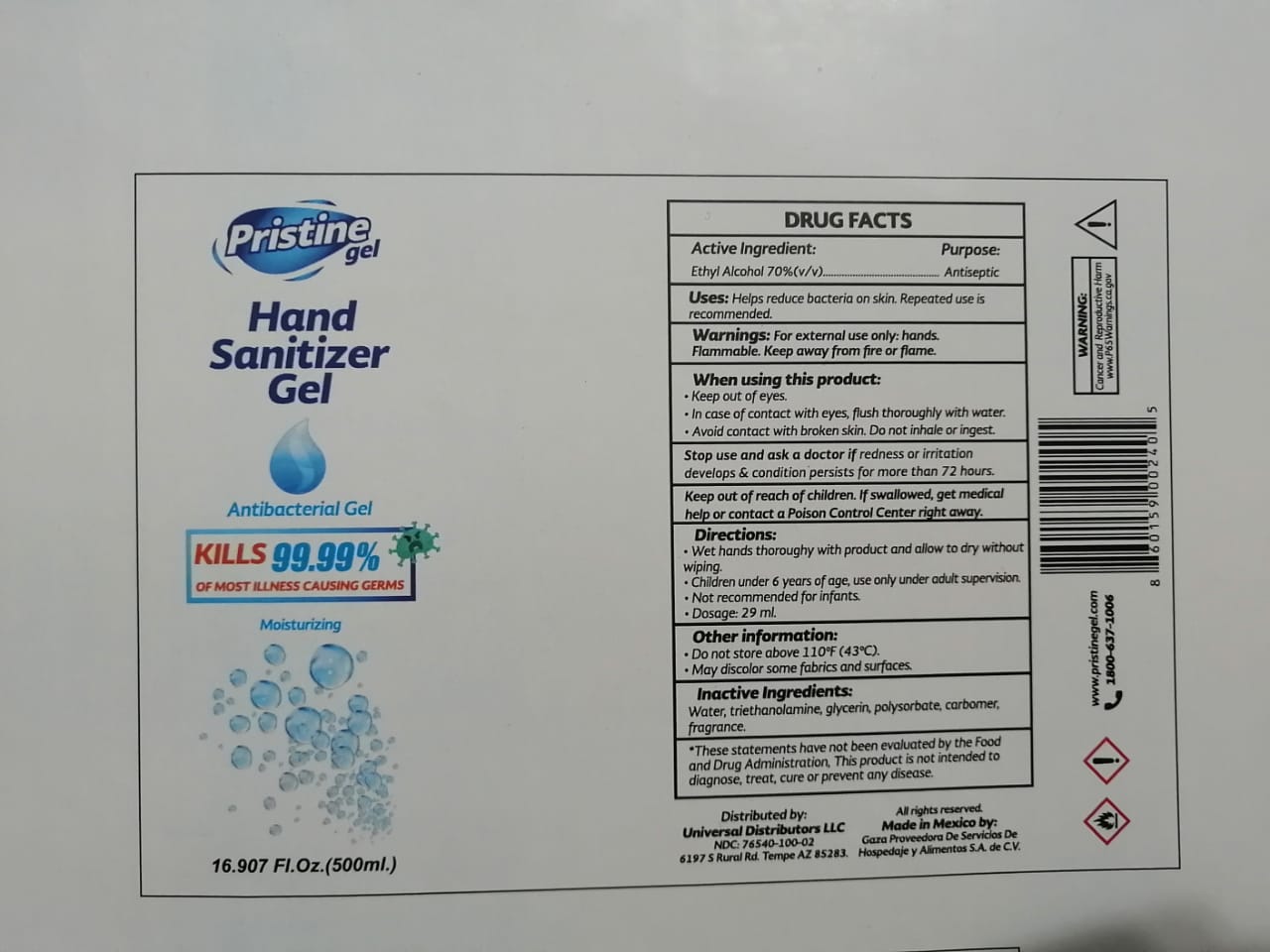 DRUG LABEL: Pristine Hand Sanitizer
NDC: 76938-001 | Form: GEL
Manufacturer: GAZA PROVEEDORA DE SERVICIOS DE HOSPEDAJE Y ALIMENTACION
Category: otc | Type: HUMAN OTC DRUG LABEL
Date: 20200714

ACTIVE INGREDIENTS: ALCOHOL 70 mL/100 mL
INACTIVE INGREDIENTS: GLYCERIN 10 mL/100 mL; POLYSORBATE 20 3.33 mL/100 mL; WATER 14.884 mL/100 mL; TROLAMINE 1.336 mL/100 mL; FRAGRANCE LAVENDER & CHIA F-153480 0.2 mL/100 mL; CARBOMER HOMOPOLYMER, UNSPECIFIED TYPE 0.25 mL/100 mL

Pristine Hand Sanitizer Gel (125, 250, 500mL)

Active Ingredient(s)

Alcohol 70% v/v. Purpose: Antiseptic

Purpose

Antiseptic, Hand Sanitizer

Use

Hand Sanitizer to help reduce bacteria that potentially can cause disease. For use when soap and water are not available.

Warnings

For external use only. Flammable. Keep away from heat or flame

Do not use

- in children less than 2 months of age
- on open skin wounds

When using this product keep out of eyes, ears, and mouth. In case of contact with eyes, rinse eyes thoroughly with water.
Stop use and ask a doctor if irritation or rash occurs. These may be signs of a serious condition.
Keep out of reach of children. If swallowed, get medical help or contact a Poison Control Center right away.

Stop use and ask a doctor if irritation or rash occurs. These may be signs of a serious condition.

Keep out of reach of children. If swallowed, get medical help or contact a Poison Control Center right away.

Directions

- Place enough product on hands to cover all surfaces. Rub hands together until dry.
- Supervise children under 6 years of age when using this product to avoid swallowing.

Other information

- Store between 15-30C (59-86F)
- Avoid freezing and excessive heat above 40C (104F)

Inactive ingredients

water, glycerin, polysorbate, triethanolamine, carbomer, fragrance

Package Label - Principal Display Panel

125 mL NDC: 76938-001-01

250 mL NDC: 76938-001-02

500 mL NDC: 76938-001-03